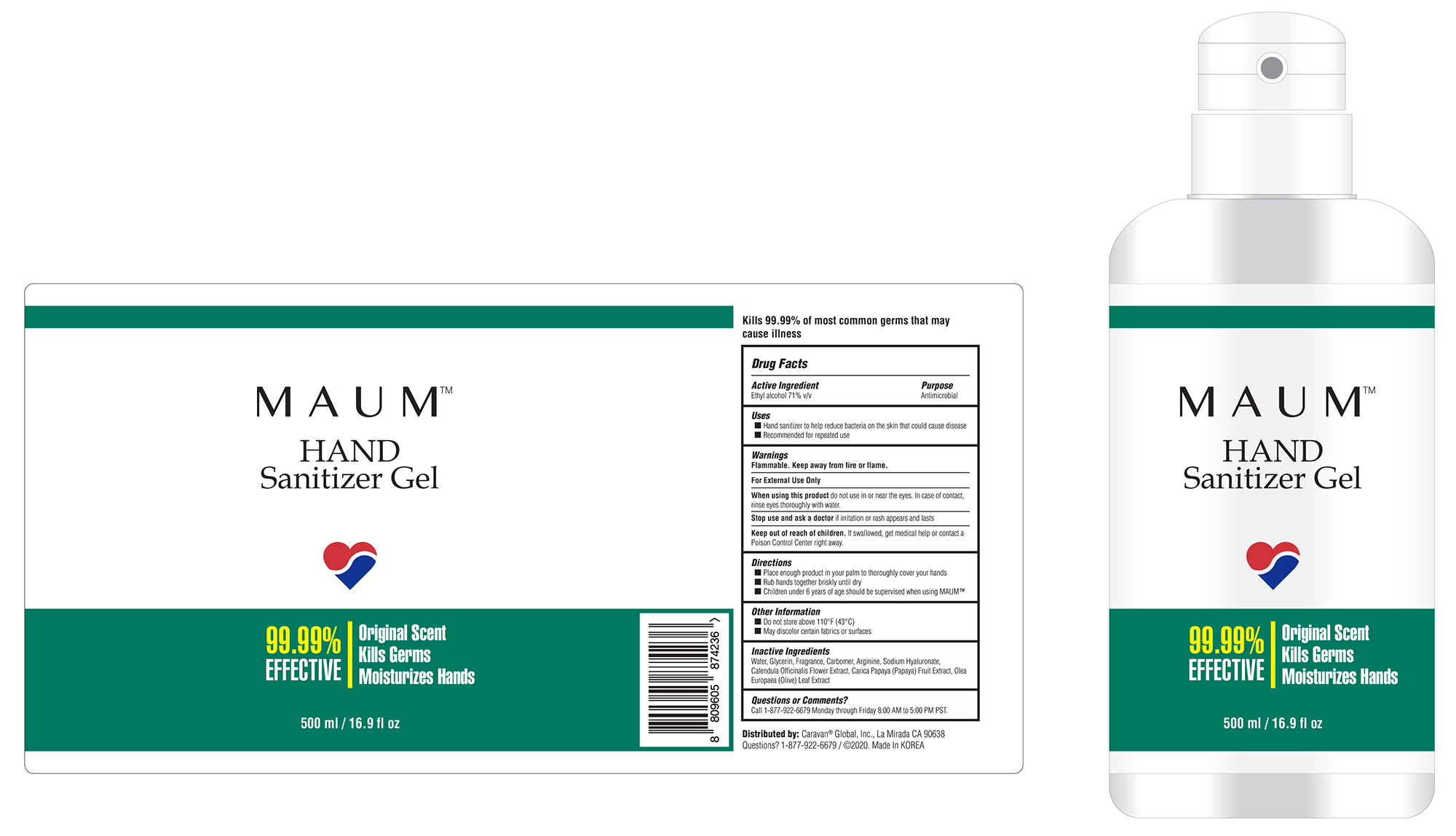 DRUG LABEL: Hand Sanitizer
NDC: 74464-001 | Form: GEL
Manufacturer: CARAVAN CANOPY INT'L INC.
Category: otc | Type: HUMAN OTC DRUG LABEL
Date: 20201117

ACTIVE INGREDIENTS: ALCOHOL 71 mL/100 mL
INACTIVE INGREDIENTS: CARBOMER 934 0.3 mL/100 mL; ARGININE; HYALURONATE SODIUM; WATER; CALENDULA OFFICINALIS FLOWER; CARICA PAPAYA LEAF; OLEA EUROPAEA LEAF; GLYCERIN 5 mL/100 mL; FRAGRANCE LAVENDER & CHIA F-153480 0.4 mL/100 mL

Hand Sanitizer

Active Ingredient(s)

Ethyl Alcohol 71% v/v. Purpose: Antimicrobial

Purpose

Antimicrobial, Hand Sanitizer

Use

Hand Sanitizer to help reduce bacteria that potentially can cause disease. For use when soap and water are not available.

Recommended for repeated use

Warnings

For external use only. Flammable. Keep away from heat or flame

Do not use

- in children less than 2 months of age
- on open skin wounds

When using this product keep out of eyes, ears, and mouth. In case of contact with eyes, rinse eyes thoroughly with water.
Stop use and ask a doctor if irritation or rash occurs. These may be signs of a serious condition.
Keep out of reach of children. If swallowed, get medical help or contact a Poison Control Center right away.

Stop use and ask a doctor if irritation or rash occurs. These may be signs of a serious condition.

Keep out of reach of children. If swallowed, get medical help or contact a Poison Control Center right away.

Directions

- Place enough product on hands to cover all surfaces. Rub hands together until dry.
- Supervise children under 6 years of age when using this product to avoid swallowing.

Other information

- Store between 15-30C (59-86F)
- Avoid freezing and excessive heat above 40C (104F)

Inactive ingredients

Water, Glycerin, Humi-fulvate, Fragrance, Carbomer, Arginine, Sodium Hyaluronate, Calendula Officinalis Flower Extract, Carica Papaya (Papaya) Fruit Extract, Olea Europaea (Olive) Leaf Extract

Package Label - Principal Display Panel

500 ml NDC: 74464-001-10